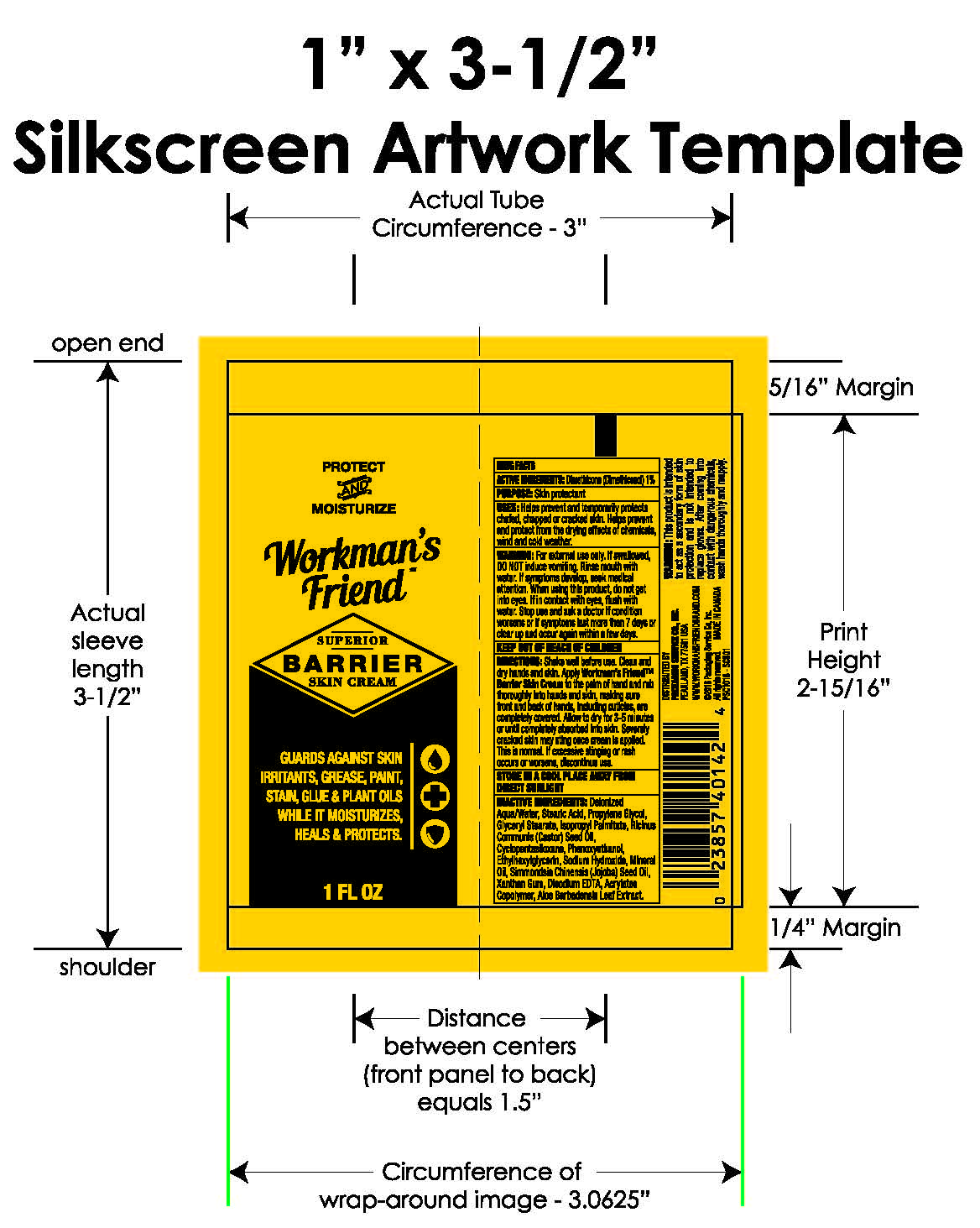 DRUG LABEL: WORKMANS FRIEND SUPERIOR BARRIER SKIN
NDC: 71810-101 | Form: CREAM
Manufacturer: SolvChem, Inc.
Category: otc | Type: HUMAN OTC DRUG LABEL
Date: 20260116

ACTIVE INGREDIENTS: DIMETHICONE 1 g/100 mL
INACTIVE INGREDIENTS: WATER; STEARIC ACID; PROPYLENE GLYCOL; GLYCERYL MONOSTEARATE; ISOPROPYL PALMITATE; CASTOR OIL; CYCLOMETHICONE 5; MINERAL OIL; PHENOXYETHANOL; JOJOBA OIL; SODIUM HYDROXIDE; ETHYLHEXYLGLYCERIN; XANTHAN GUM; ALOE VERA LEAF; BUTYL ACRYLATE/METHYL METHACRYLATE/METHACRYLIC ACID COPOLYMER (18000 MW)

WORKMAN'S FRIEND SUPERIOR BARRIER SKIN CREAM

ACTIVE INGREDIENT(S)

DIMETHICONE (DIMETHICONOL) 1%

PURPOSE

SKIN PROTECTANT

USES

Helps prevent and temporarily protects chafed, chapped or cracked skin. Helps prevent and protect from the drying effects of chemicals, wind and cold weather.

Keep out of reach of children.

WARNINGS

For external use only. If swallowed, do NOT induce vomiting. Rinse mouth with water. If symptoms develop seek medical attention. When using this product, do not get into eyes. If in contact with eyes flush with water. Stop use and ask a doctor if condition worsens symptoms last more than 7 days or clear up and occur again within a few days.

DIRECTIONS

Shake well before use. Clean and dry hands and skin. Apply Workman's Friend™ Barrier Skin Cream to the palm of hand and rub thoroughly into hands and skin, making sure front and back of hands, including cuticles, are completely covered. Allow to dry for 3-5 minutes or until completely absorbed into skin. Severely cracked skin may sting once cream is applied. This is normal. If excessive stinging or rash occurs or worsens, discontinue use.

Other:

STORE IN A COOL PLACE AWAY FROM DIRECT SUNLIGHT

Inactive Ingredients:

Deionized Aqua/Water, Stearic Acid, Propylene Glycol, Glyceryl Stearate, Isopropyl Palmitate, Ricinus Communis (Castor) Seed Oil, Cyclopentasiloxane, Phenoxyethanol, Ethylhexylglycerin, Sodium Hydroxide, Mineral Oil, Simmondsia Chinensis (Jojoba) Seed Oil, Xanthan Gum, Disodium EDTA, Acrylates Copolymer, Aloe Barbadensis Leaf Extract.